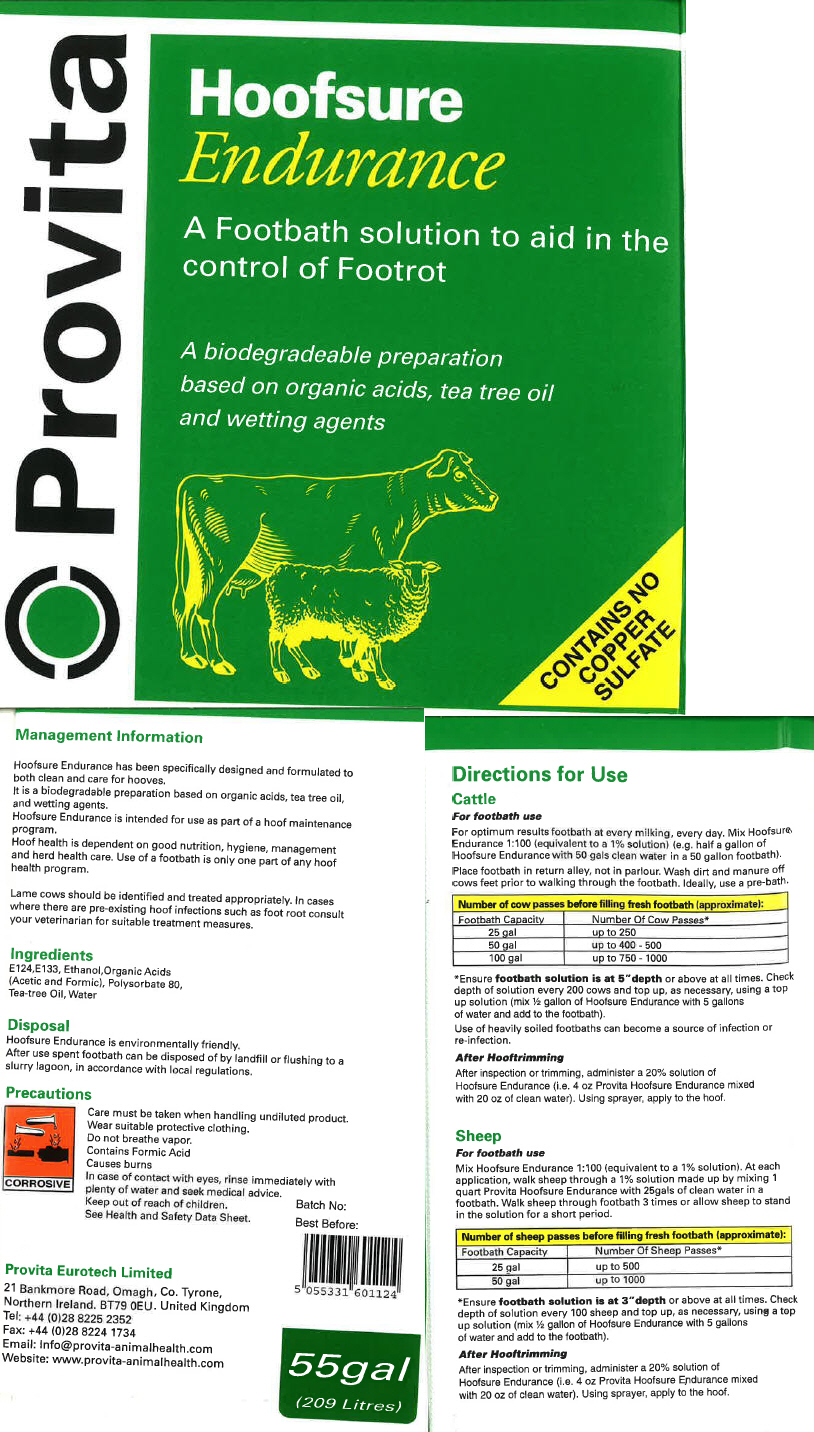 DRUG LABEL: Provita 
NDC: 16371-103 | Form: SOLUTION, CONCENTRATE
Manufacturer: Provita Eurotech Ltd
Category: animal | Type: OTC ANIMAL DRUG LABEL
Date: 20151208

ACTIVE INGREDIENTS: FORMIC ACID 608 g/1 L

Hoofsure
Endurance

Management Information

Hoofsure Endurance has been specifically designed and formulated to both clean and care for hooves.

It is a biodegradable preparation based on organic acids, tea tree oil, and wetting agents.

Hoofsure Endurance is intended for use as part of a hoof maintenance program.

Hoof health is dependent on good nutrition, hygiene, management and herd health care. Use of a footbath is only one part of any hoof health program.

Lame cows should he identified and treated appropriately. In cases where there are pre-existing hoof infections such as foot root consult your veterinarian for suitable treatment measures.

ACTIVE INGREDIENT

Ingredients

E124, E133, Ethanol, Organic Acids (Acetic and Formic), Polysorbate 80, Tea-tree Oil, Water

Disposal

Hoofsure Endurance is environmentally friendly. After use spent footbath can be disposed of by landfill or flushing to a slurry lagoon, in accordance with local regulations.

Precautions

Care must be taken when handling undiluted product.

Wear suitable protective clothing.

Do not breathe vapor.

Contains Formic Acid

Causes burns

In case of contact with eyes, rinse immediately with plenty of water and seek medical advice.

Keep out of reach of children.

See Health and Safety Data Sheet.

CORROSIVE

Directions for Use

Cattle

For footbath use

For optimum results footbath at every milking, every day. Mix Hoofsure Endurance 1:100 (equivalent to a 1% solution) (e.g. half a gallon of Hoofsure Endurance with 50 gals clean water in a 50 gallon footbath). Place footbath in return alley, not in parlour. Wash dirt and manure off cows feet prior to walking through the footbath. Ideally, use a pre-bath.

Number of cow passes before filling fresh footbath (approximate):
Footbath Capacity | Number Of Cow Passes [Ensure footbath solution is at 5"depth or above at all times. Check depth of solution every 200 cows and top up, as necessary, using a top up solution (mix ½ gallon of Hoofsure Endurance with 5 gallons of water and add to the footbath).]
25 gal | up to 250
50gal | up to 400-500
100 gal | up to 750 -- 1000

Use of heavily soiled footbaths can become a source of infection or re-infection.

After Hooftrimming

After inspection or trimming, administer a 20% solution of Hootsure Endurance (i.e. 4 oz Provita Hoofsure Endurance mixed with 20 oz of clean water). Using sprayer, apply to the hoof.

Sheep

For footbath use

Mix Hoofsure Endurance 1:100 (equivalent to a 1% solution). At each application, walk sheep through a 1% solution made up by mixing 1 quart Provita Hoofsure Endurance with 25gals of clean water in a footbath. Walk sheep through footbath 3 times or allow sheep to stand in the solution for a short period.

Number of sheep passes before filling fresh footbath (approximate):
Footbath Capacity | Number Of Sheep Passes [Ensure footbath solution is at 3"depth or above at all times. Check depth of solution every 100 sheep and top up, as necessary, using a top up solution (mix ½ gallon of Hoofsure Endurance with 5 gallons of water and add to the footbath).]
25 gal | Up to 500
50 gal | Up to 1000

After Hooftrimming

After inspection or trimming, administer a 20% solution of Hoofsure Endurance (i.e. 4 oz Provita Hoofsure Endurance mixed with 20 oz of clean water). Using sprayer, apply to the hoof.

PRINCIPAL DISPLAY PANEL - Drum Label

Provita

Hoofsure
Endurance

A Footbath solution to aid in the
control of Footrot

A biodegradeable preparation
based on organic acids, tea tree oil
and wetting agents

CONTAINS NO
COPPER
SULFATE